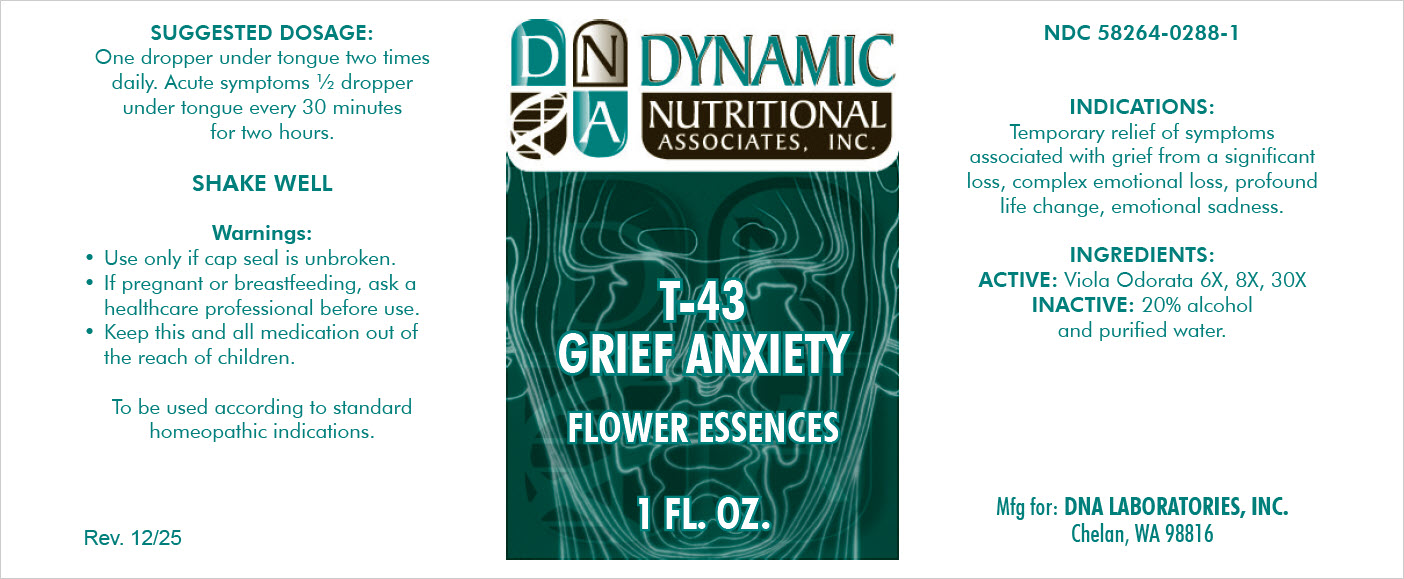 DRUG LABEL: T-43
NDC: 58264-0288 | Form: SOLUTION
Manufacturer: DNA Labs, Inc.
Category: homeopathic | Type: HUMAN OTC DRUG LABEL
Date: 20251217

ACTIVE INGREDIENTS: VIOLA ODORATA FLOWER 30 [hp_X]/1 mL
INACTIVE INGREDIENTS: WATER; ALCOHOL

T-43

NDC 58264-0288-1

INDICATIONS

PURPOSE

Temporary relief of symptoms associated with grief from a significant loss, complex emotional loss, profound life change, emotional sadness.

ACTIVE

Viola Odorata 6X, 8X, 30X

INACTIVE

20% alcohol and purified water.

DOSAGE AND ADMINISTRATION

One dropper under tongue two times daily. Acute symptoms 1/2 dropper under tongue every 30 minutes for two hours.

STORAGE AND HANDLING

SHAKE WELL

WARNINGS

Use only if cap seal is unbroken.

PREGNANCY OR BREAST FEEDING

If pregnant or breastfeeding, ask a healthcare professional before use.

KEEP OUT OF REACH OF CHILDREN

Keep this and all medication out of the reach of children.

To be used according to standard homeopathic indications.

PACKAGE LABEL

DYNAMIC

NUTRITIONAL

ASSOCIATES

T-43

GRIEF ANXIETY

FLOWER ESSENCES

1 FL. OZ.